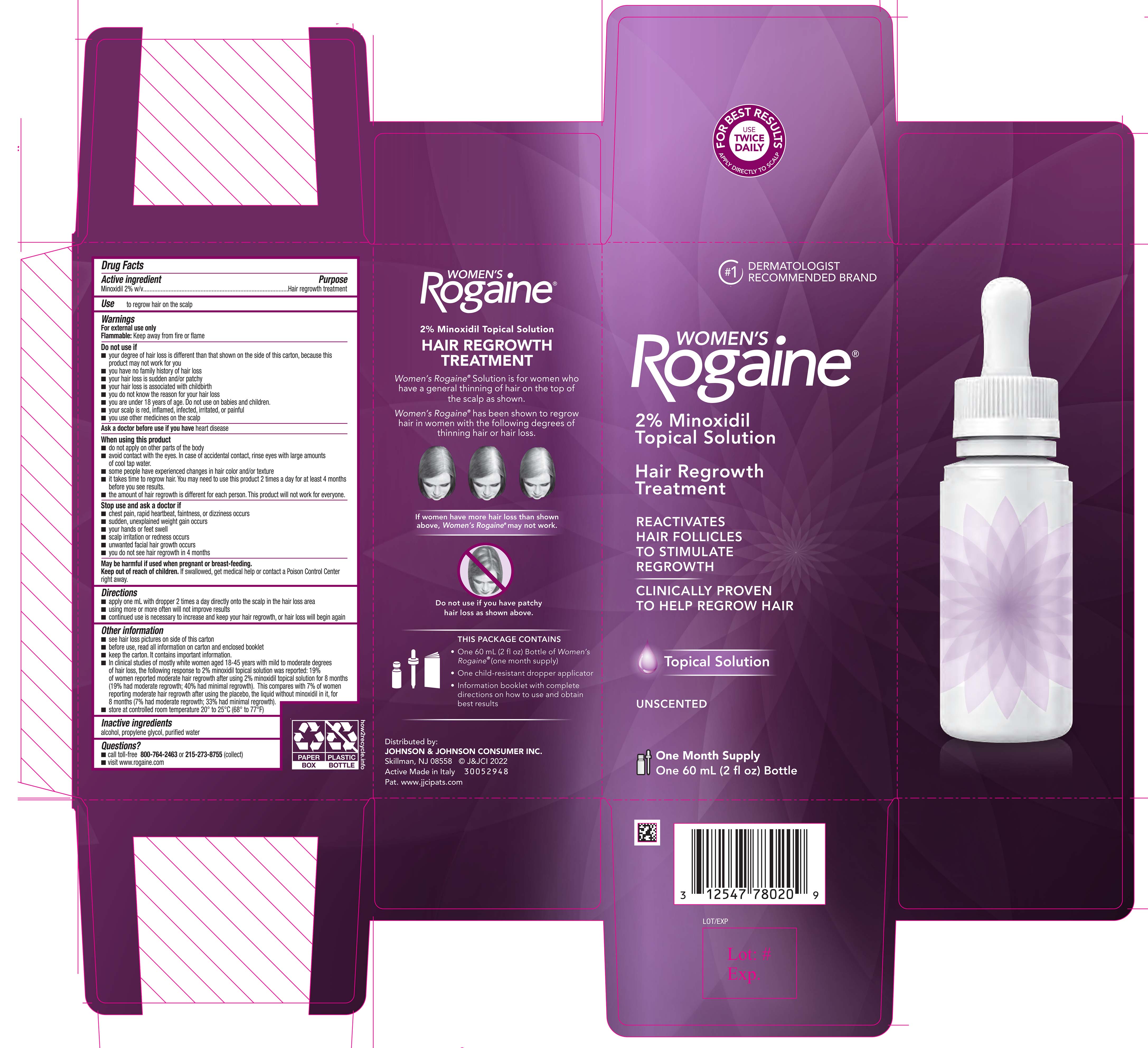 DRUG LABEL: Womens Rogaine Unscented
NDC: 69968-0090 | Form: SOLUTION
Manufacturer: Kenvue Brands LLC
Category: otc | Type: HUMAN OTC DRUG LABEL
Date: 20240906

ACTIVE INGREDIENTS: MINOXIDIL 20 mg/1 mL
INACTIVE INGREDIENTS: ALCOHOL; PROPYLENE GLYCOL; WATER

WOMEN'S Rogaine® UNSCENTED

Drug Facts

Active ingredient

Minoxidil 2% w/v

Purpose

Hair regrowth treatment

Use

to regrow hair on the scalp

Warnings

For external use only

Flammable: Keep away from fire or flame

Do not use if

- your degree of hair loss is different than that shown on the side of this carton, because this product may not work for you
- you have no family history of hair loss
- your hair loss is sudden and/or patchy
- your hair loss is associated with childbirth
- you do not know the reason for your hair loss
- you are under 18 years of age. Do not use on babies and children.
- your scalp is red, inflamed, infected, irritated, or painful
- you use other medicines on the scalp

Ask a doctor before use if you have heart disease

When using this product

- do not apply on other parts of the body
- avoid contact with the eyes. In case of accidental contact, rinse eyes with large amounts of cool tap water.
- some people have experienced changes in hair color and/or texture
- it takes time to regrow hair. You may need to use this product 2 times a day for at least 4 months before you see results.
- the amount of hair regrowth is different for each person. This product will not work for everyone.

Stop use and ask a doctor if

- chest pain, rapid heartbeat, faintness, or dizziness occurs
- sudden, unexplained weight gain occurs
- your hands or feet swell
- scalp irritation or redness occurs
- unwanted facial hair growth occurs
- you do not see hair regrowth in 4 months

PREGNANCY OR BREAST FEEDING

May be harmful if used when pregnant or breast-feeding.

Keep out of reach of children. If swallowed, get medical help or contact a Poison Control Center right away.

Directions

- apply one mL with dropper 2 times a day directly onto the scalp in the hair loss area
- using more or more often will not improve results
- continued use is necessary to increase and keep your hair regrowth, or hair loss will begin again

Other information

- see hair loss pictures on side of this carton
- before use, read all information on carton and enclosed booklet
- keep the carton. It contains important information.
- In clinical studies of mostly white women aged 18-45 years with mild to moderate degrees of hair loss, the following response to 2% minoxidil topical solution was reported: 19% of women reported moderate hair regrowth after using 2% minoxidil topical solution for 8 months (19% had moderate regrowth; 40% had minimal regrowth). This compares with 7% of women reporting moderate hair regrowth after using the placebo, the liquid without minoxidil in it, for 8 months (7% had moderate regrowth; 33% had minimal regrowth).
- store at controlled room temperature 20° to 25° C (68° to 77° F)

Inactive ingredients

alcohol, propylene glycol, purified water

Questions?

- call toll-free 800-764-2463 or 215-273-8755 (collect)
- visit www.rogaine.com

Distributed by:

JOHNSON & JOHNSON CONSUMER INC.

Skillman, NJ 08558

PRINCIPAL DISPLAY PANEL - 60 mL Bottle Carton

#1 DERMATOLOGIST

RECOMMENDED BRAND

WOMEN’S

Rogaine®

2% Minoxidil

Topical Solution

Hair Regrowth

Treatment

REACTIVATES

HAIR FOLLICLES

TO STIMULATE

REGROWTH

CLINICALLY PROVEN

TO HELP REGROW HAIR

Topical Solution

UNSCENTED

One Month Supply

One 60 mL (2 fl oz) Bottle